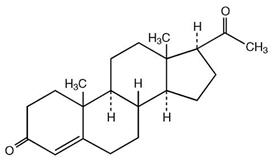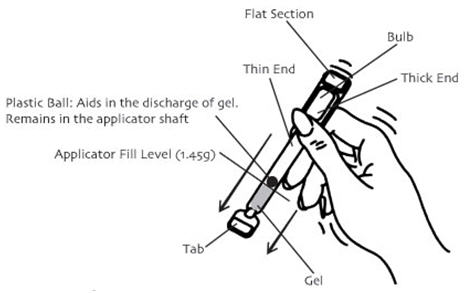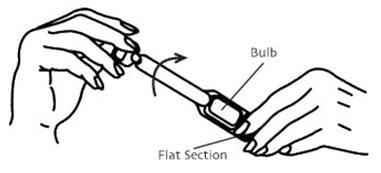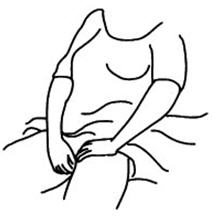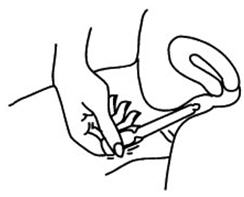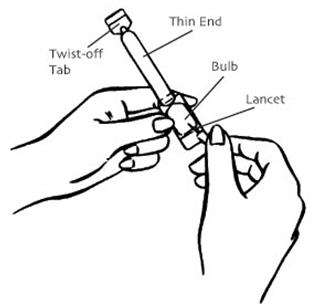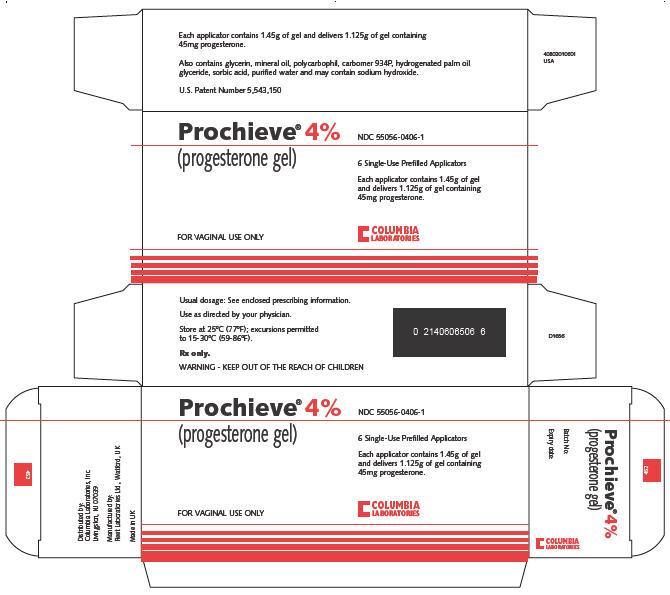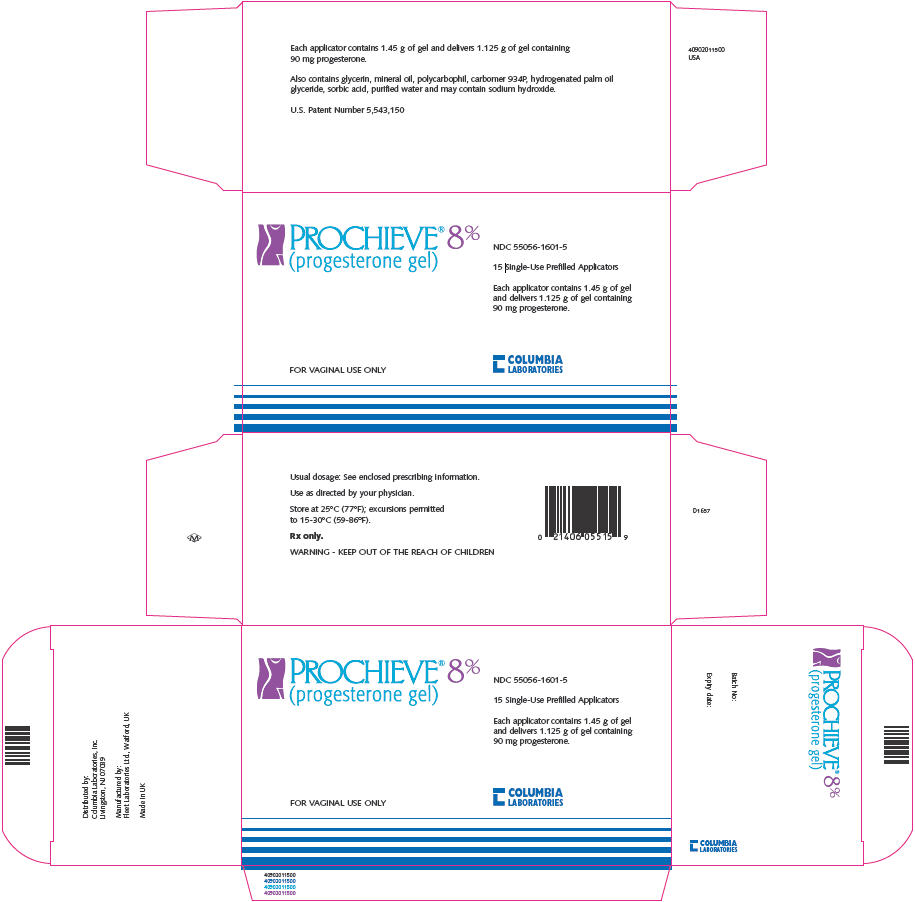 DRUG LABEL: Prochieve
NDC: 55056-0406 | Form: GEL
Manufacturer: Columbia Laboratories
Category: prescription | Type: HUMAN PRESCRIPTION DRUG LABEL
Date: 20091119

ACTIVE INGREDIENTS: progesterone 45 mg/1.125 g
INACTIVE INGREDIENTS: glycerin; mineral oil; polycarbophil; carbomer 934; hydrogenated palm oil; sorbic acid; water; sodium hydroxide

Prochieve® 4%
Prochieve® 8%
(progesterone gel)

DESCRIPTION

Prochieve® (progesterone gel) is a bioadhesive vaginal gel containing micronized progesterone in an emulsion system, which is contained in single use, one piece polyethylene vaginal applicators. The carrier vehicle is an oil in water emulsion containing the water swellable, but insoluble polymer, polycarbophil. The progesterone is partially soluble in both the oil and water phase of the vehicle, with the majority of the progesterone existing as a suspension. Physically, Prochieve® has the appearance of a soft, white to off-white gel.

The active ingredient, progesterone, is present in either a 4% or an 8% concentration (w/w). The chemical name for progesterone is pregn-4-ene-3,20-dione. It has an empirical formula of C21H30O2 and a molecular weight of 314.5.

The structural formula is:

Progesterone exists in two polymorphic forms. Form 1, which is the form used in Prochieve®, exists as white orthorhombic prisms with a melting point of 127-131°C.

Each applicator delivers 1.125 grams of Prochieve® gel containing either 45 mg (4% gel) or 90 mg (8% gel) of progesterone in a base containing glycerin, mineral oil, polycarbophil, carbomer 934P, hydrogenated palm oil glyceride, sorbic acid, purified water and may contain sodium hydroxide.

CLINICAL PHARMACOLOGY

Progesterone is a naturally occurring steroid that is secreted by the ovary, placenta, and adrenal gland. In the presence of adequate estrogen, progesterone transforms a proliferative endometrium into a secretory endometrium. Progesterone is essential for the development of decidual tissue, and the effect of progesterone on the differentiation of glandular epithelia and stroma has been extensively studied. Progesterone is necessary to increase endometrial receptivity for implantation of an embryo. Once an embryo is implanted, progesterone acts to maintain the pregnancy. Normal or near-normal endometrial responses to oral estradiol and intramuscular progesterone have been noted in functionally agonadal women through the sixth decade of life. Progesterone administration decreases the circulatory levels of gonadotropins.

Pharmacokinetics

Absorption

Due to the sustained release properties of Prochieve®, progesterone absorption is prolonged with an absorption half-life of approximately 25-50 hours, and an elimination half-life of 5-20 minutes. Therefore, the pharmacokinetics of Prochieve® are rate-limited by absorption rather than by elimination.

The bioavailability of progesterone in Prochieve® was determined relative to progesterone administered intramuscularly. In a single dose crossover study, 20 healthy, estrogenized postmenopausal women received 45 mg or 90 mg progesterone vaginally in Prochieve® 4% or Prochieve® 8%, or 45 mg or 90 mg progesterone intramuscularly. The pharmacokinetic parameters (mean ± standard deviation) are shown in Table 1.

TABLE 1 Single Dose Relative Bioavailability
 | PROCHIEVE® 4% | 45 mg Intramuscular Progesterone | PROCHIEVE® 8% | 90 mg Intramuscular Progesterone
Cmax (ng/mL) | 13.15±6.49 | 39.06±13.68 | 14.87±6.32 | 53.76±14.9
Cavg 0-24 (ng/mL) | 6.94±4.24 | 22.41±4.92 | 6.98±3.21 | 28.98±8.75
AUC0-96 (ng∙hr/mL) | 288.63±273.72 | 806.26±102.75 | 296.78±129.90 | 1378.91±176.39
Tmax (hr) | 5.6±1.84 | 8.2±6.43 | 6.8±3.3 | 9.2±2.7
t1/2 (hr) | 55.13±28.04 | 28.05±16.87 | 34.8±11.3 | 19.6±6.0
F (%) | 27.6 |  | 19.8
Cmax - maximum progesterone serum concentration
Cavg 0-24 - average progesterone serum concentration over 24 hours
AUC0-96 - area under the drug concentration versus time curve from 0-96 hours post dose
Tmax - time to maximum progesterone concentration
t1/2 - elimination half-life
F - relative bioavailability

The multiple dose pharmacokinetics of Prochieve® 4% and Prochieve® 8% administered every other day and Prochieve® 8% administered daily or twice daily for 12 days were studied in 10 healthy, estrogenized postmenopausal women in two separate studies. Steady state was achieved within the first 24 hours after initiation of treatment. The pharmacokinetic parameters (mean ± standard deviation) after the last administration of Prochieve® 4% or 8% derived from these studies are shown in Table 2.

TABLE 2 Multiple Dose Pharmacokinetics
 | Assisted Reproductive Technology |  | Secondary Amenorrhea
 | Daily Dosing 8% | Twice Daily Dosing 8% | Every Other Day Dosing 4% | Every Other Day Dosing 8%
Cmax (ng/mL) | 15.97± 5.05 | 14.57 ± 4.49 | 13.21± 9.46 | 13.67 ± 3.58
Cavg (ng/mL) | 8.99 ± 3.53 | 11.6 ± 3.47 | 4.05 ± 2.85 | 6.75 ± 2.83
Tmax (hr) | 5.40 ± 0.97 | 3.55 ± 2.48 | 6.67 ± 3.16 | 7.00 ± 2.88
AUC0-t (ng∙hr/mL) | 391.98 ±153.28 | 138.72 ± 41.58 | 242.15 ± 167.88 | 438.36 ± 223.36
t1/2 (hr) | 45.00 ± 34.70 | 25.91 ± 6.15 | 49.87 ± 31.20 | 39.08 ± 12.88

Distribution

Progesterone is extensively bound to serum proteins (~96-99%), primarily to serum albumin and corticosteroid binding globulin.

Metabolism

The major urinary metabolite of oral progesterone is 5β-pregnan-3α, 20α-diol glucuronide which is present in plasma in the conjugated form only. Plasma metabolites also include 5β-pregnan-3α-ol-20-one (5β-pregnanolone) and 5α-pregnan-3α-ol-20-one (5β-pregnanolone).

Excretion

Progesterone undergoes both biliary and renal elimination. Following an injection of labeled progesterone, 50-60% of the excretion of progesterone metabolites occurs via the kidney; approximately 10% occurs via the bile and feces, the second major excretory pathway. Overall recovery of labeled material accounts for 70% of an administered dose, with the remainder of the dose not characterized with respect to elimination. Only a small portion of unchanged progesterone is excreted in the bile.

Clinical Studies

Assisted Reproductive Technology

In a single-center, open-label study (COL1620-007US), 99 women (aged 28-47 years) with either partial (n=84) or premature ovarian failure (n=15) who were candidates to receive a donor oocyte transfer as an Assisted Reproductive Technology ("ART") procedure were randomized to receive either Prochieve® 8% twice daily (n=68) or intramuscular progesterone 100 mg daily (n=31). The study was divided into three phases (Pilot, Donor Egg and Treatment). The first phase of the study consisted of a test Pilot Cycle to ensure that the administration of transdermal estradiol and progesterone would adequately prime the endometrium to receive the donor egg. The second phase was the Donor Egg Cycle during which a fertilized oocyte was implanted. Prochieve® 8% was administered beginning the evening of Day 14 of the Pilot and Donor Egg cycles. Subjects with partial ovarian function also underwent a Pre-Pilot Cycle and a Pre-Donor Egg Cycle during which time they were administered only leuprolide acetate to suppress remaining ovarian function. The Pre-Pilot Cycle, Pilot Cycle, Pre-Donor Egg Cycle, and Donor Egg Cycle each lasted approximately 34 days. The third phase of the study consisted of a 10-week treatment period to maintain a pregnancy until placental autonomy was achieved.

Sixty-one women received Prochieve® 8% as part of the Pilot Cycle to determine their endometrial response. Of the 55 evaluable endometrial biopsies in the Prochieve® 8% group performed on Day 25-27, all were histologically "in-phase", consistent with luteal phase biopsy specimens of menstruating women at comparable time intervals. Fifty-four women who received Prochieve® 8% and had a histologically "in-phase" biopsy received a donor oocyte transfer. Among these 54 Prochieve®-treated women, clinical pregnancies (assessed about week 10 after transfer by clinical examination, ultrasound and/or ß-hCG levels) occurred in 26 women (48%). Seventeen women (31%) delivered a total of 25 newborns, seven women (13%) had spontaneous abortions and two women (4%) had elective abortions.

In a second study (COL1620-F01), Prochieve® 8% was used in luteal phase support of women with tubal or idiopathic infertility due to endometriosis and normal ovulatory cycles, undergoing in vitro fertilization ("IVF") procedures. All women received a GnRH analog to suppress endogenous progesterone, human menopausal gonadotropins, and human chorionic gonadotropin. In this multi-center, open-label study, 139 women (aged 22-38 years) received Prochieve® 8% once daily beginning within 24 hours of embryo transfer and continuing through Day 30 post-transfer. Clinical pregnancies assessed at Day 90 post-transfer were seen in 36 (26%) of women. Thirty-two women (23%) delivered newborns and four women (3%) had spontaneous abortions. (See PRECAUTIONS, subsection Pregnancy)

Secondary Amenorrhea

In three parallel, open-label studies (COL1620-004US, COL1620-005US, COL1620-009US), 127 women (aged 18-44) with hypothalamic amenorrhea or premature ovarian failure were randomized to receive either Prochieve® 4% (n=62) or Prochieve® 8% (n=65). All women were treated with either conjugated estrogens 0.625 mg daily (n=100) or transdermal estradiol (delivering 50 mcg/day) twice weekly (n=27).

Estrogen therapy was continuous for the entire three 28-day cycle studies. At Day 15 of the second cycle (six weeks after initiating estrogen replacement), women who demonstrated adequate response to estrogen therapy (by ultrasound) and who continued to be amenorrheic received Prochieve® every other day for six doses (Day 15 through Day 25 of the cycle).

In cycle 2, Prochieve® 4% induced bleeding in 79% of women and Prochieve® 8% induced bleeding in 77% of women. In the third cycle, estrogen was continued and Prochieve® was administered every other day beginning on Day 15 for six doses. On Day 24 an endometrial biopsy was performed. In 53 women who received Prochieve® 4%, biopsy results were as follows: 7% proliferative, 40% late secretory, 19% mid secretory, 13% early secretory, 7% atrophic, 6% menstrual endometrium, 6% inactive endometrium and 2% negative endometrium. In 54 women who received Prochieve® 8%, biopsy results were as follows: 44% late secretory, 19% mid secretory, 11% early secretory, 19% atrophic, 5% menstrual endometrium and 2% "oral contraceptive like" endometrium.

INDICATIONS AND USAGE

Assisted Reproductive Technology

Prochieve® 8% is indicated for progesterone supplementation or replacement as part of an Assisted Reproductive Technology ("ART") treatment for infertile women with progesterone deficiency.

Secondary Amenorrhea

Prochieve® 4% is indicated for the treatment of secondary amenorrhea. Prochieve® 8% is indicated for use in women who have failed to respond to treatment with Prochieve® 4%.

CONTRAINDICATIONS

Prochieve® should not be used in individuals with any of the following conditions:

1. Known sensitivity to Prochieve® (progesterone or any of the other ingredients)
2. Undiagnosed vaginal bleeding
3. Liver dysfunction or disease
4. Known or suspected malignancy of the breast or genital organs
5. Missed abortion
6. Active thrombophlebitis or thromboembolic disorders, or a history of hormone-associated thrombophlebitis or thromboembolic disorders

WARNINGS

The physician should be alert to the earliest manifestations of thrombotic disorders (thrombophlebitis, cerebrovascular disorders, pulmonary embolism, and retinal thrombosis). Should any of these occur or be suspected, the drug should be discontinued immediately.

Progesterone and progestins have been used to prevent miscarriage in women with a history of recurrent spontaneous pregnancy losses. No adequate evidence is available to show that they are effective for this purpose.

PRECAUTIONS

General

1. The pretreatment physical examination should include special reference to breast and pelvic organs, as well as Papanicolaou smear.
2. In cases of breakthrough bleeding, as in all cases of irregular vaginal bleeding, nonfunctional causes should be considered. In cases of undiagnosed vaginal bleeding, adequate diagnostic measures should be undertaken.
3. Because progestogens may cause some degree of fluid retention, conditions which might be influenced by this factor (e.g., epilepsy, migraine, asthma, cardiac or renal dysfunction) require careful observation.
4. The pathologist should be advised of progesterone therapy when relevant specimens are submitted.
5. Patients who have a history of psychic depression should be carefully observed and the drug discontinued if the depression recurs to a serious degree.
6. A decrease in glucose tolerance has been observed in a small percentage of patients on estrogen-progestin combination drugs. The mechanism of this decrease is not known. For this reason, diabetic patients should be carefully observed while receiving progestin therapy.

Information for Patients

The product should not be used concurrently with other local intravaginal therapy. If other local intravaginal therapy is to be used concurrently, there should be at least a 6-hour period before or after Prochieve® administration. Small, white globules may appear as a vaginal discharge possibly due to gel accumulation, even several days after usage.

Drug Interactions

No drug interactions have been assessed with Prochieve®.

Carcinogenesis, Mutagenesis, Impairment of Fertility

Nonclinical toxicity studies to determine the potential of Prochieve® to cause carcinogenicity or mutagenicity have not been performed. The effect of Prochieve® on fertility has not been evaluated in animals.

Pregnancy

(See CLINICAL PHARMACOLOGY, subsection Clinical Studies)

Prochieve® 8% has been used to support embryo implantation and maintain pregnancies through its use as part of ART treatment regimens in two clinical studies (studies COL1620-007US and COL1620-F01). In the first study (COL1620-007US), 54 Prochieve®-treated women had donor oocyte transfer procedures, and clinical pregnancies occurred in 26 women (48%). The outcomes of these 26 pregnancies were as follows: one woman had an elective termination of pregnancy at 19 weeks due to congenital malformations (omphalocele) associated with a chromosomal abnormality; one woman pregnant with triplets had an elective termination of her pregnancy; seven women had spontaneous abortions; and 17 women delivered 25 apparently normal newborns.

In the second study (COL1620-F01), Prochieve® 8% was used in the luteal phase support of women undergoing in vitro fertilization ("IVF") procedures. In this multi-center, open-label study, 139 women received Prochieve® 8% once daily beginning within 24 hours of embryo transfer and continuing through Day 30 post-transfer.

Clinical pregnancies assessed at Day 90 post-transfer were seen in 36 (26%) of women. Thirty-two women (23%) delivered newborns and four women (3%) had spontaneous abortions. Of the 47 newborns delivered, one had a teratoma associated with a cleft palate; one had respiratory distress syndrome; 44 were apparently normal and one was lost to follow-up.

Geriatric Use

The safety and effectiveness in geriatric patients (over age 65) have not been established.

Pediatric Use

Safety and effectiveness in pediatric patients have not been established.

Nursing Mothers

Detectable amounts of progestins have been identified in the milk of mothers receiving them. The effect of this on the nursing infant has not been determined.

ADVERSE REACTIONS

Assisted Reproductive Technology

In a study of 61 women with ovarian failure undergoing a donor oocyte transfer procedure receiving Prochieve® 8% twice daily, treatment-emergent adverse events occurring in 5% or more of the women are shown in Table 3.

TABLE 3 Treatment-Emergent Adverse Events in ≥5% of Women Receiving Prochieve® 8% Twice Daily Study COL1620-007US (n=61)
Body as a Whole
Bloating | 7%
Cramps NOS | 15%
Pain | 8%
Central and Peripheral Nervous System
Dizziness | 5%
Headache | 13%
Gastro-Intestinal System
Nausea | 7%
Reproductive, Female
Breast Pain | 13%
Moniliasis Genital | 5%
Vaginal Discharge | 7%
Skin and Appendages
Pruritus Genital | 5%

In a second clinical study of 139 women using Prochieve® 8% once daily for luteal phase support while undergoing an in vitro fertilization procedure, treatment-emergent adverse events reported in ≥5% of the women are shown in Table 4.

TABLE 4 Treatment-Emergent Adverse Events in ≥5% of Women Receiving Prochieve® 8% Once Daily Study COL1620-F01 (n=139)
Body as a Whole
Abdominal Pain | 12%
Perineal Pain Female | 17%
Central and Peripheral Nervous System
Headache | 17%
Gastro-Intestinal System
Constipation | 27%
Diarrhea | 8%
Nausea | 22%
Vomiting | 5%
Musculo-Skeletal System
Arthralgia | 8%
Psychiatric
Depression | 11%
Libido Decreased | 10%
Nervousness | 16%
Somnolence | 27%
Reproductive, Female
Breast Enlargement | 40%
Dyspareunia | 6%
Urinary System
Nocturia | 13%

Secondary Amenorrhea

In three studies, 127 women with secondary amenorrhea received estrogen replacement therapy and Prochieve® 4% or 8% every other day for six doses. Treatment emergent adverse events during estrogen and Prochieve® treatment that occurred in 5% or more of women are shown in Table 5.

TABLE 5 Treatment-Emergent Adverse Events in ≥5% of Women Receiving Estrogen Treatment and Prochieve® Every Other Day Studies COL1620-004US, COL1620-005US, COL1620-009US
 | Estrogen + Prochieve® 4% n=62 | Estrogen + Prochieve® 8% n=65
Body as a Whole
Abdominal Pain | 3 (5%) | 6 (9%)
Appetite Increased | 3 (5%) | 5 (8%)
Bloating | 8 (13%) | 8 (12%)
Cramps NOS | 12 (19%) | 17 (26%)
Fatigue | 13 (21%) | 14 (22%)
Central and Peripheral Nervous System
Headache | 12 (19%) | 10 (15%)
Gastro-Intestinal System
Nausea | 5 (8%) | 4 (6%)
Musculo-Skeletal System
Back Pain | 5 (8%) | 2 (3%)
Myalgia | 5.(8%) | 0 (0%)
Psychiatric
Depression | 12 (19%) | 10 (15%)
Emotional Lability | 14 (23%) | 14 (22%)
Sleep Disorder | 11 (18%) | 12 (18%)
Reproductive, Female
Vaginal Discharge | 7 (11%) | 2 (3%)
Resistance Mechanism
Upper Respiratory Tract Infection | 3 (5%) | 5 (8%)
Skin and Appendages
Pruitis genital | 1 (2%) | 4 (6%)

Additional adverse events reported in women at a frequency <5% in Prochieve® ART and secondary amenorrhea studies and not listed in the tables above include:

Autonomic Nervous System–mouth dry, sweating increased

Body as a Whole–abnormal crying, allergic reaction, allergy, appetite decreased, asthenia, edema, face edema, fever, hot flushes, influenza-like symptoms, water retention, xerophthalmia

Cardiovascular, General–syncope

Central and Peripheral Nervous System–migraine, tremor

Gastro-Intestinal–dyspepsia, eructation, flatulence, gastritis, toothache

Metabolic and Nutritional–thirst

Musculo-Skeletal System–cramps legs, leg pain, skeletal pain

Neoplasm–benign cyst

Platelet, Bleeding & Clotting–purpura

Psychiatric–aggressive reactions, forgetfulness, insomnia

Red Blood Cell–anemia

Reproductive, Female–dysmenorrhea, premenstrual tension, vaginal dryness

Resistance Mechanism–infection, pharyngitis, sinusitis, urinary tract infection

Respiratory System–asthma, dyspnea, hyperventilation, rhinitis

Skin and Appendages–acne, pruritis, rash, seborrhea, skin discoloration, skin disorder, urticaria

Urinary System–cystitis, dysuria, micturition frequency

Vision Disorders–conjunctivitis

OVERDOSAGE

There have been no reports of overdosage with Prochieve®. In the case of overdosage, however, discontinue Prochieve®, treat the patient symptomatically, and institute supportive measures.

As with all prescription drugs, this medicine should be kept out of the reach of children.

DOSAGE AND ADMINISTRATION

Assisted Reproductive Technology

Prochieve® 8% is administered vaginally at a dose of 90 mg once daily in women who require progesterone supplementation. Prochieve® 8% is administered vaginally at a dose of 90 mg twice daily in women with partial or complete ovarian failure who require progesterone replacement. If pregnancy occurs, treatment may be continued until placental autonomy is achieved, up to 10-12 weeks.

Secondary Amenorrhea

Prochieve® 4% is administered vaginally every other day up to a total of six doses. For women who fail to respond, a trial of Prochieve® 8% every other day up to a total of six doses may be instituted.

It is important to note that a dosage increase from the 4% gel can only be accomplished by using the 8% gel. Increasing the volume of gel administered does not increase the amount of progesterone absorbed.

SEE Prochieve® PATIENT INFORMATION SHEET - HOW TO USE Prochieve®.
Note: The PATIENT INFORMATION SHEET contains special instructions for using the applicator at altitudes above 2500 feet in order to avoid a partial release of Prochieve® before vaginal insertion.

HOW SUPPLIED

Prochieve® is available in the following strengths:

4% gel (45 mg) in a single use, one piece, disposable, white polyethylene vaginal applicator with a twist-off top. Each applicator contains 1.45 g of gel and delivers 1.125 g of gel.

NDC-55056-0406-1 - 6 Single-use prefilled applicators.

8% gel (90 mg) in a single use, one piece, disposable, white polyethylene vaginal applicator with a twist-off top. Each applicator contains 1.45 g of gel and delivers 1.125 g of gel.

NDC-55056-1601-6 - 6 Single-use prefilled applicators
NDC-55056-1601-5 - 15 Single-use prefilled applicators
NDC-55056-1601-8 - 18 Single-use prefilled applicators

Each applicator is wrapped and sealed in a foil overwrap.

STORAGE AND HANDLING

Store at 25°C (77°F); excursions permitted to 15-30°C (59-86°F).

Rx only.

U.S. Patent Number 5,543,150.

Manufactured for: Columbia Laboratories, Inc. Livingston, NJ 07039

Manufactured by: Fleet Laboratories Ltd., Watford, United Kingdom

Revised May 2009

PATIENT INFORMATION

Prochieve® 8%
(progesterone gel)
For Vaginal Use Only

FOR PROGESTERONE SUPPLEMENTATION OR REPLACEMENT AS PART OF AN ASSISTED REPRODUCTIVE TECHNOLOGY ("ART") TREATMENT FOR INFERTILE WOMEN WITH PROGESTERONE DEFICIENCY

Please read this information carefully before you start to use Prochieve® and each time your prescription is renewed, in case anything has changed. This leaflet does not take the place of discussions with your doctor. If you still have any questions, ask your doctor or health-care provider.

What Prochieve® is

Prochieve® is a specially formulated gel that you insert in your vagina. It contains the natural female hormone called progesterone. Prochieve® 8% is used as part of a program for women who are undergoing fertility treatment.

Understanding the role of Prochieve® in your infertility treatment

Progesterone is one of the hormones essential for maintaining a pregnancy. If you are undergoing ART treatment and your doctor has determined your body does not produce enough progesterone on its own, Prochieve® may be prescribed to provide the progesterone you need.

The progesterone in Prochieve® will help prepare the lining of your uterus so that it is ready to receive and nourish a fertilized egg. If pregnancy occurs, Prochieve® may be supplemented for 10-12 weeks until production of progesterone by the placenta is adequate.

When you should not use Prochieve®

- If you are allergic to progesterone, progesterone-like drugs, or any of the inactive ingredients in the gel (ask a pharmacist if you are not sure about the inactive ingredients in Prochieve®).
- If you have unusual vaginal bleeding which has not been evaluated by a doctor.
- If you have a liver disease.
- If you have known or suspected cancer of the breast or genital organs.
- If you have a miscarriage and your physician suspects some tissue is still in the uterus.
- If you have or have had blood clots in the legs, lungs, eyes, or elsewhere.

Risks of Prochieve®

- Risk to the fetus. Birth defects have been reported in the offspring of women who were using Prochieve® during early pregnancy. These included an abdominal wall defect and a cleft palate. A causal association has been neither confirmed nor refuted. You should check with your doctor about the risks to your unborn child of any medication used during pregnancy.
- Blood clots and related health problems. Blood clots have been reported with the use of estrogens and progestational drugs (alone or in combination). If blood clots do form in your bloodstream, they can cut off the blood supply to vital organs, causing serious problems. These problems may include a stroke (by cutting off blood to part of the brain), a heart attack (by cutting off blood to part of the heart), a pulmonary embolus (by cutting off blood to part of the lungs), or other problems. Any of these conditions may cause death or serious long-term disability. Call your doctor immediately if you suspect you have any of these conditions. He or she may advise you to stop using this drug.

PRECAUTIONS

Be alert for unusual signs and symptoms. If any of these warning signals (or any other unusual symptoms) happen while you are using Prochieve®, call your doctor immediately:

- Abnormal bleeding from the vagina.
- Pains in the calves or chest, a sudden shortness of breath or coughing blood indicating possible clots in the legs, heart, or lungs.
- Severe headache or vomiting, dizziness, faintness, or changes in vision or speech, weakness or numbness of an arm or leg indicating possible clots in the brain or eye.
- Breast lumps, which could be associated with fibrocystic disorders, fibroadenoma, or breast cancer. (Ask your doctor or health-care provider to show you how to examine your breasts monthly.)
- Yellowing of the skin and/or white of the eyes indicating possible liver problems.

You should also notify your doctor if you experience depression, worsening of your diabetic condition, or fluid retention.

Possible side effects of Prochieve®

In addition to the risks listed above, the following side effects have been reported with Prochieve® used either for progesterone supplementation or for replacement as part of an ART treatment for infertile women with progesterone deficiency. Consult your doctor if you experience any of the side effects mentioned below, or other side effects.

SIDE EFFECTS REPORTED AT A FREQUENCY OF 5% OR GREATER

- abdominal pain; perineal pain (the perineum is the area between the vagina and the rectum)
- headache
- constipation; diarrhea; nausea
- joint pain
- depression; decreased libido; nervousness; sleepiness [If you experience dizziness or sleepiness, do not drive or operate machinery.]
- breast enlargement
- excessive urination at night

SIDE EFFECTS REPORTED AT A FREQUENCY RANGING FROM 1% TO 5%

- allergy; bloating; cramps; fatigue; pain
- dizziness
- vomiting
- mood swings
- breast pain
- difficult or painful intercourse; genital itching; genital yeast infection; vaginal discharge
- urinary tract infection

SIDE EFFECTS REPORTED AT A FREQUENCY OF LESS THAN 1%

- fever; flu-like symptoms
- water retention [This may worsen some conditions such as asthma, epilepsy, migraine, heart disease, or kidney disease.]
- gastrointestinal discomfort; gas; abdominal swelling
- back pain; leg pain
- insomnia
- sinusitis; upper respiratory tract infection
- asthma
- acne; itching
- painful or difficult urination; frequent urination

How Prochieve® works

Prochieve® has been formulated to be administered through the vagina. The moisturizing gel in Prochieve® forms a coating on the walls of the vagina which allows for absorption of progesterone through the vaginal tissue. Small, white globules may appear as a vaginal discharge possibly due to gel accumulation, even several days after usage. Prochieve® contains no irritating perfumes or dyes.

Other information

1. Your doctor has prescribed this drug for you and you alone. Do not give this drug to anyone else.
2. This medication was prescribed for your particular medical condition. Do not use it for another condition.
3. Keep this and all drugs out of the reach of children.

How to use Prochieve®

The dosage is one application of the 8% gel (90 mg of progesterone) vaginally, daily or twice daily as directed by your doctor. If you become pregnant, your doctor may decide to continue treatment for up to 10 to 12 weeks.

Prochieve® is to be applied directly from the specially designed sealed applicator into the vagina. The applicator is designed to deliver a premeasured dose of Prochieve®. A small amount of gel will be left in the tube after usage. Do not be concerned because you will still be receiving the appropriate, measured dosage.

Under certain rare circumstances, such as high altitude, brief exposure to high temperature, sudden changes in atmospheric/barometric pressure, and pressure controlled environments such as airplanes or high-rise buildings, the internal pressure of the applicator may become higher than the air pressure. This imbalance between the internal and external pressure may cause the gel to expel from the applicator when the twist-off tab is removed. If you should experience the gel expelling from the applicator upon opening, please follow the SPECIAL INSTRUCTIONS FOR USE AT ALTITUDES ABOVE 2500 FEET.

1. Remove the applicator from the sealed wrapper. DO NOT remove the twist-off tab at this time. For use at altitudes above 2500 feet, see special instructions below.
2. Hold the applicator between the thumb and forefinger along the seam on the sides of the bulb. Shake down vigorously 3 to 4 times (like a thermometer) to ensure that the contents are at the thin end of the applicator.
3. Hold the applicator by the flat section of the bulb. Twist off the tab at the thin end and throw away. DO NOT squeeze the bulb while twisting the tab. This could force some gel to be released before it is inserted.
  Twist off completely – Do not pull off
4. The applicator may be inserted into the vagina while you are in a sitting position or when lying on your back with your knees bent. Gently insert the thin end well into the vagina.
5. Squeeze the bulb of the applicator to deposit the gel into the vagina. Remove the applicator and throw it away in a waste container. Do not be concerned if a small amount of gel is left in the applicator. You will still be receiving the appropriate, measured dosage.

SPECIAL INSTRUCTIONS FOR USE AT ALTITUDES ABOVE 2500 FEET

1. Remove the applicator from the sealed wrapper. DO NOT remove the twist-off tab at this time. Hold the applicator on both sides of the bulb, as shown. Using a lancet or a stick pin, make a single puncture in the flat part of the bulb. This will relieve the difference in air pressure between the inside and outside of the applicator caused by high altitudes. It will not affect the amount of gel administered. You will still be receiving the appropriate, measured dosage.
2. See Step 2 above.
3. See Step 3 above.
4. See Step 4 above.
5. Place your thumb or finger over the puncture that you made in the bulb of the applicator. Squeeze the bulb of the applicator to deposit the gel into the vagina. Remove the applicator and throw it away in a waste container. Do not be concerned if a small amount of gel is left in the applicator. You will still be receiving the appropriate, measured dosage.

Prochieve® coats the vaginal lining to provide long-lasting release of progesterone. Small, white globules may appear as a vaginal discharge possibly due to gel accumulation, even several days after usage. It is not unusual, but if you are concerned, discuss this with your doctor.

If you forget a dose of Prochieve®, use it as soon as you remember, but do not use more than the recommended daily dose. Prochieve® should not be used at the same time that you are using other vaginal therapy.

This leaflet provides the most important information about Prochieve®. If you want to read more, ask your doctor or pharmacist about the professional leaflet. You may need their help to understand some of the information.

How Supplied

Prochieve® is available in two strengths: 4% gel (45 mg of progesterone) and 8% gel (90 mg of progesterone).

Each box of the 4% gel contains six single use, disposable vaginal applicators with a twist-off tab. Each box of the 8% gel contains either six, fifteen, or eighteen single use, disposable vaginal applicators with a twist-off tab. Each applicator is wrapped and sealed in a foil overwrap.

Prochieve® should be stored at 25°C (77°F); excursions permitted to 15-30°C (59-86°F).

Do not use Prochieve® after the expiration date which is printed on the box.

Manufactured for: Columbia Laboratories, Inc., Livingston, NJ 07039

Manufactured by: Fleet Laboratories Ltd., Watford, United Kingdom

Revised May 2009

PATIENT INFORMATION

Prochieve® 4% and Prochieve® 8% (progesterone gel)
For Vaginal Use Only

FOR THE TREATMENT OF SECONDARY AMENORRHEA (ABSENCE OF MENSES IN WOMEN WHO HAVE PREVIOUSLY HAD A MENSTRUAL PERIOD)

Please read this information carefully before you start to use Prochieve® and each time your prescription is renewed, in case anything has changed. This leaflet does not take the place of discussions with your doctor. If you still have any questions, ask your doctor or health-care provider.

What Prochieve® is

Prochieve® is a specially formulated gel that you insert in your vagina. It contains the natural female hormone called progesterone. The 4% gel is used for women whose menstrual cycle has stopped. The 8% gel is to be used when the 4% gel has not worked.

Understanding the role of Prochieve® in the treatment of your menstrual irregularities

Progesterone is one of the hormones essential for regular menstrual periods. If your doctor has determined your body does not produce enough progesterone on its own, Prochieve® may be prescribed to provide the progesterone you need.

When you do not produce enough progesterone, menstrual irregularities can occur. Prochieve® can provide you with the progesterone needed during a normal menstrual cycle.

When you should not use Prochieve®

- If you are allergic to progesterone, progesterone-like drugs, or any of the inactive ingredients in the gel (ask a pharmacist if you are not sure about the inactive ingredients in Prochieve®).
- If you have unusual vaginal bleeding which has not been evaluated by a doctor.
- If you have a liver disease.
- If you have known or suspected cancer of the breast or genital organs.
- If you have a miscarriage and your physician suspects some tissue is still in the uterus.
- If you have or have had blood clots in the legs, lungs, eyes, or elsewhere.

Risks of Prochieve®

- Risk to the fetus. Birth defects have been reported in the offspring of women who were using Prochieve® during early pregnancy. These included an abdominal wall defect and a cleft palate. A causal association has been neither confirmed nor refuted. You should check with your doctor about the risks to your unborn child of any medication used during pregnancy.
- Blood clots and related health problems. Blood clots have been reported with the use of estrogens and progestational drugs (alone or in combination). If blood clots do form in your bloodstream, they can cut off the blood supply to vital organs, causing serious problems. These problems may include a stroke (by cutting off blood to part of the brain), a heart attack (by cutting off blood to part of the heart), a pulmonary embolus (by cutting off blood to part of the lungs), or other problems. Any of these conditions may cause death or serious long-term disability. Call your doctor immediately if you suspect you have any of these conditions. He or she may advise you to stop using this drug.

PRECAUTIONS

Be alert for unusual signs and symptoms. If any of these warning signals (or any other unusual symptoms) happen while you are using Prochieve®, call your doctor immediately:

- Abnormal bleeding from the vagina.
- Pains in the calves or chest, a sudden shortness of breath or coughing blood indicating possible clots in the legs, heart, or lungs.
- Severe headache or vomiting, dizziness, faintness, or changes in vision or speech, weakness or numbness of an arm or leg indicating possible clots in the brain or eye.
- Breast lumps, which could be associated with fibrocystic disorders, fibroadenoma, or breast cancer. (Ask your doctor or health-care provider to show you how to examine your breasts monthly.)
- Yellowing of the skin and/or white of the eyes indicating possible liver problems.

You should also notify your doctor if you experience depression, worsening of your diabetic condition, or fluid retention.

Possible side effects of Prochieve®

In addition to the risks listed above, the following side effects have been reported in studies with Prochieve® used for the treatment of menstrual irregularities due to progesterone deficiency. In these studies, women were treated with estrogen prior to and during Prochieve® therapy. All side effects reported at a frequency of 5% or greater after Prochieve® was added to estrogen therapy also were reported with estrogen therapy alone. Consult your doctor if you experience any of the side effects mentioned below, or other side effects.

SIDE EFFECTS REPORTED AT A FREQUENCY OF 5% OR GREATER

- abdominal pain; increased appetite; bloating; cramps; fatigue
- headache
- nausea
- back pain
- depression; mood swings; sleep disorder
- vaginal discharge
- upper respiratory tract infection

SIDE EFFECTS REPORTED AT A FREQUENCY RANGING FROM 1% TO 5%

- increased sweating
- allergy; flu-like symptoms; hot flushes; pain
- dizziness [If you experience dizziness or sleepiness, do not drive or operate machinery.]
- migraine; tremor
- gas; gastrointestinal discomfort
- thirst
- leg pain; muscle pain
- insomnia; nervousness; sleepiness
- breast pain; painful menstruation
- infection; genital yeast infection
- acne; genital itching; rash; skin disorder
- frequent urination

SIDE EFFECTS REPORTED AT A FREQUENCY OF LESS THAN 1%

- dry mouth
- abnormal crying; allergic reaction; decreased appetite; dry eyes; swelling; face swelling; perineal pain (the perineum is the area between the vagina and the rectum); water retention [This may worsen some conditions such as asthma, epilepsy, migraine, heart disease, or kidney disease.] ; weakness
- fainting
- abdominal swelling; gastritis; toothache
- joint pain; leg cramps; skeletal pain
- non-cancerous cyst
- bruising
- aggressive reaction; forgetfulness
- anemia
- premenstrual syndrome; vaginal dryness
- sore throat
- rapid, shallow breathing; shortness of breath; runny nose
- hives; itching; oily or dry scaly skin; skin discoloration
- bladder inflammation; painful or difficult urination
- "pink eye"

How Prochieve® works

Prochieve® has been formulated to be administered through the vagina. The moisturizing gel in Prochieve® forms a coating on the walls of the vagina which allows for absorption of progesterone through the vaginal tissue. Small, white globules may appear as a vaginal discharge possibly due to gel accumulation, even several days after usage. Prochieve® contains no irritating perfumes or dyes.

Other information

1. Your doctor has prescribed this drug for you and you alone. Do not give this drug to anyone else.
2. This medication was prescribed for your particular medical condition. Do not use it for another condition.
3. Keep this and all drugs out of the reach of children.

How to use Prochieve®

The dosage is one application of the 4% gel (45 mg of progesterone), vaginally, every other day as directed by your doctor, for a total of six doses. In some cases, your doctor may prescribe the 8% gel (90 mg of progesterone) every other day, for a total of six doses.

It is important to note that a dosage increase from the 4% gel can only be accomplished by using the 8% gel. Increasing the volume of gel administered does not increase the amount of progesterone absorbed.

Prochieve® is to be applied directly from the specially designed sealed applicator into the vagina. The applicator is designed to deliver a premeasured dose of Prochieve®. A small amount of gel will be left in the tube after usage. Do not be concerned because you will still be receiving the appropriate, measured dosage.

Under certain rare circumstances, such as high altitude, brief exposure to high temperature, sudden changes in atmospheric/barometric pressure, and pressure controlled environments such as airplanes or high-rise buildings, the internal pressure of the applicator may become higher than the air pressure. This imbalance between the internal and external pressure may cause the gel to expel from the applicator when the twist-off tab is removed. If you should experience the gel expelling from the applicator upon opening, please follow the SPECIAL INSTRUCTIONS FOR USE AT ALTITUDES ABOVE 2500 FEET.

1. Remove the applicator from the sealed wrapper. DO NOT remove the twist-off tab at this time. For use at altitudes above 2500 feet, see special instructions below.
2. Hold the applicator between the thumb and forefinger along the seam on the sides of the bulb. Shake down vigorously 3 to 4 times (like a thermometer) to ensure that the contents are at the thin end of the applicator.
3. Hold the applicator by the flat section of the bulb. Twist off the tab at the thin end and throw away. DO NOT squeeze the bulb while twisting the tab. This could force some gel to be released before it is inserted.
  Twist off completely – Do not pull off
4. The applicator may be inserted into the vagina while you are in a sitting position or when lying on your back with your knees bent. Gently insert the thin end well into the vagina.
5. Squeeze the bulb of the applicator to deposit the gel into the vagina. Remove the applicator and throw it away in a waste container. Do not be concerned if a small amount of gel is left in the applicator. You will still be receiving the appropriate, measured dosage.

SPECIAL INSTRUCTIONS FOR USE AT ALTITUDES ABOVE 2500 FEET

1. Remove the applicator from the sealed wrapper. DO NOT remove the twist-off tab at this time. Hold the applicator on both sides of the bulb, as shown. Using a lancet or a stick pin, make a single puncture in the flat part of the bulb. This will relieve the difference in air pressure between the inside and outside of the applicator caused by high altitudes. It will not affect the amount of gel administered. You will still be receiving the appropriate, measured dosage.
2. See Step 2 above.
3. See Step 3 above.
4. See Step 4 above.
5. Place your thumb or finger over the puncture that you made in the bulb of the applicator. Squeeze the bulb of the applicator to deposit the gel into the vagina. Remove the applicator and throw it away in a waste container. Do not be concerned if a small amount of gel is left in the applicator. You will still be receiving the appropriate, measured dosage.

Prochieve® coats the vaginal lining to provide long-lasting release of progesterone. Small, white globules may appear as a vaginal discharge possibly due to gel accumulation, even several days after usage. It is not unusual, but if you are concerned, discuss this with your doctor.

If you forget a dose of Prochieve®, use it as soon as you remember, but do not use more than the recommended daily dose. Prochieve® should not be used at the same time that you are using other vaginal therapy.

This leaflet provides the most important information about Prochieve®. If you want to read more, ask your doctor or pharmacist about the professional leaflet. You may need their help to understand some of the information.

How Supplied

Prochieve® is available in two strengths: 4% gel (45 mg of progesterone) and 8% gel (90 mg of progesterone).

Each box of the 4% gel contains six single use, disposable vaginal applicators with a twist-off tab. Each box of the 8% gel contains either six, fifteen, or eighteen single use, disposable vaginal applicators with a twist-off tab. Each applicator is wrapped and sealed in a foil overwrap.

Prochieve® should be stored at 25°C (77°F); excursions permitted to 15-30°C (59-86°F).

Do not use Prochieve® after the expiration date which is printed on the box.

Manufactured for: Columbia Laboratories, Inc., Livingston, NJ 07039

Manufactured by: Fleet Laboratories Ltd., Watford, United Kingdom

Revised May 2009

PRINCIPAL DISPLAY PANEL - 4% / 6 Single-Use Prefilled Applicator Carton

Prochieve® 4%
(progesterone gel)

NDC 55056-0406-1

6 Single-Use Prefilled Applicators

Each applicator contains 1.45g of gel
and delivers 1.125g of gel containing
45mg progesterone.

FOR VAGINAL USE ONLY

COLUMBIA
LABORATORIES

PRINCIPAL DISPLAY PANEL - 8% / 15 Single-Use Prefilled Applicator Carton

PROCHIEVE® 8%
(progesterone gel)

NDC 55056-1601-5

15 Single-Use Prefilled Applicators

Each applicator contains 1.45 g of gel
and delivers 1.125 g of gel containing
90 mg progesterone.

FOR VAGINAL USE ONLY

COLUMBIA
LABORATORIES